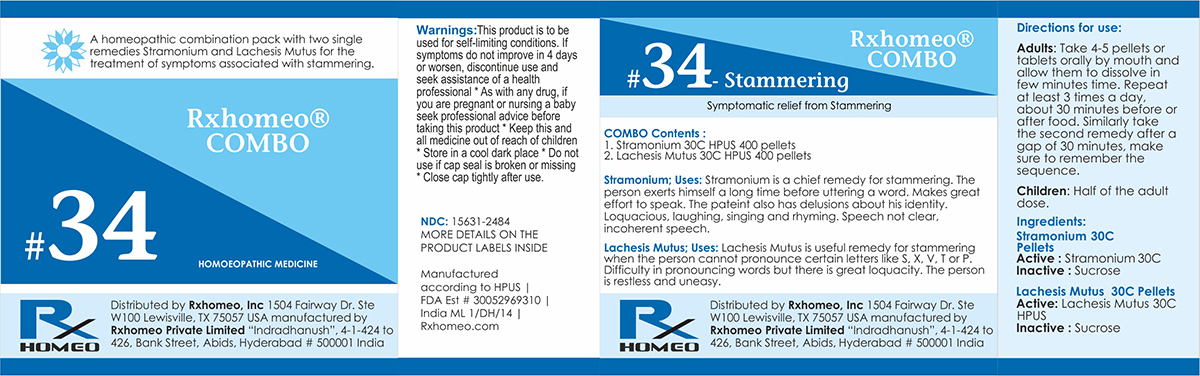 DRUG LABEL: Rxhomeo Homeopathic Combo-34
NDC: 15631-2484 | Form: KIT | Route: ORAL
Manufacturer: Rxhomeo Private Limited d.b.a.
Category: homeopathic | Type: HUMAN OTC DRUG LABEL
Date: 20161127

ACTIVE INGREDIENTS: DATURA STRAMONIUM 6 [hp_X]/1 1; LACHESIS MUTA VENOM 8 [hp_X]/1 1
INACTIVE INGREDIENTS: SUCROSE; LACTOSE

ACTIVE INGREDIENT

STRAMONIUM HPUS 6X and higher

LACHESIS MUTUS HPUS 8X and higher

USES

A homeopathic combination pack with two single remedies Stramonium and Lachesis Mutus for the treatment of symptoms associated with stammering.
Stramonium;Uses: Stramonium is a chief remedy for stammering. The person exerts himself a long time before uttering a word. Makes great effort to speak. The pateint also has delusions about his identity. Loquacious, laughing, singing and rhyming. Speech not clear, incoherent speech.

Lachesis Mutus;Uses: Lachesis Mutus is useful remedy for stammering when the person cannot pronounce certain letters like S, X, V, T or P. Difficulty in pronouncing words but there is great loquacity. The person is restless and uneasy.

INDICATIONS

Condition listed above or as directed by the physician

DOSAGE

PELLETS included in the Combo

Adults- Take 4 or 6 Pellets by mouth, three times daily or as suggested by physician. Children 2 years and older- take 1/2 the adult dose.

WARNINGS

This product is to be used for self-limiting conditions

STOP USE

If symptoms do not improve in 4 days, or worsen, discontinue use and seek assistance of health professional

KEEP OUT OF REACH OF CHILDREN

Keep this and all medication out of reach of children

Do not use if capseal is broken or missing.

Close the cap tightly after use.

INACTIVE INGREDIENTS

Sucrose for Pellets

STORAGE

Store in a cool dark place

QUESTIONS OR COMMENTS

www.Rxhomeo.com | 1.888.2796642 | info@rxhomeo.com
Rxhomeo, Inc 1504 Fairway Dr. Ste W 100 Lewisville, TX 75057 USA